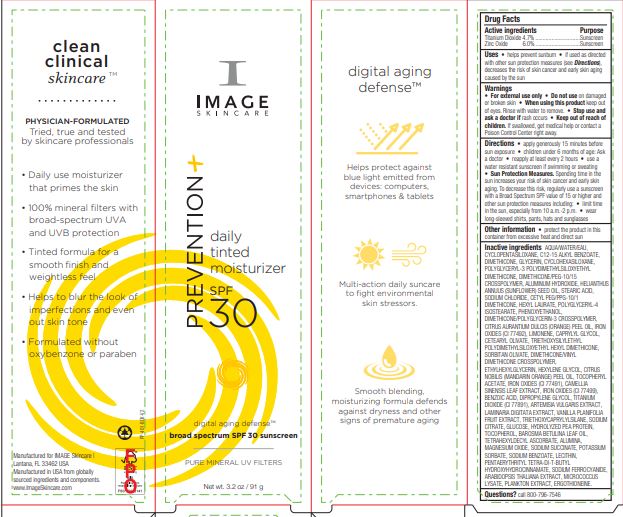 DRUG LABEL: Prevention Daily Tinted Moisturizer SPF 30
NDC: 62742-4221 | Form: CREAM
Manufacturer: Allure Labs
Category: otc | Type: HUMAN OTC DRUG LABEL
Date: 20241209

ACTIVE INGREDIENTS: TITANIUM DIOXIDE 4.7 g/100 g; ZINC OXIDE 6 g/100 g
INACTIVE INGREDIENTS: CYCLOMETHICONE 6; DIMETHICONE/POLYGLYCERIN-3 CROSSPOLYMER; STEARIC ACID; SODIUM CHLORIDE; CETYL PEG/PPG-10/1 DIMETHICONE (HLB 4); POLYGLYCERYL-4 ISOSTEARATE; PHENOXYETHANOL; ORANGE OIL; FERRIC OXIDE RED; BENZOIC ACID; TOCOPHEROL; AGATHOSMA BETULINA LEAF OIL; MAGNESIUM OXIDE; SODIUM SUCCINATE ANHYDROUS; POTASSIUM SORBATE; SODIUM BENZOATE; PENTAERYTHRITOL TETRAKIS(3-(3,5-DI-TERT-BUTYL-4-HYDROXYPHENYL)PROPIONATE); SODIUM FERROCYANIDE; GREEN TEA LEAF; WATER; CYCLOMETHICONE 5; GLYCERIN; POLYGLYCERYL-3 POLYDIMETHYLSILOXYETHYL DIMETHICONE (4000 MPA.S); ALUMINUM HYDROXIDE; MANDARIN OIL; TETRAHEXYLDECYL ASCORBATE; PEA PROTEIN; FERROSOFERRIC OXIDE; LECITHIN, SOYBEAN; ERGOTHIONEINE; HEXYL LAURATE; CAPRYLYL GLYCOL; SORBITAN OLIVATE; ALUMINUM OXIDE; DIMETHICONE/PEG-10/15 CROSSPOLYMER; SUNFLOWER OIL; LAMINARIA DIGITATA; .ALPHA.-TOCOPHEROL ACETATE; HEXYLENE GLYCOL; ARTEMISIA VULGARIS ROOT; SODIUM CITRATE; MICROCOCCUS LUTEUS; DIMETHICONE; ALKYL (C12-15) BENZOATE; FERRIC OXIDE YELLOW; LIMONENE, (+)-; ARABIDOPSIS THALIANA; DIPROPYLENE GLYCOL; TRIETHOXYSILYLETHYL POLYDIMETHYLSILOXYETHYL HEXYL DIMETHICONE; DIMETHICONE/VINYL DIMETHICONE CROSSPOLYMER (SOFT PARTICLE); ETHYLHEXYLGLYCERIN; ANHYDROUS DEXTROSE; CETEARYL OLIVATE; VANILLA; TRIETHOXYCAPRYLYLSILANE

Drug Facts

Active ingredients

Titanium Dioxide 4.7%

Zinc Oxide 6.0%

Purpose

Sunscreen

Indication and usage

Helps prevent sunburn • if used as directed with other sun protection measures (see Directions), decreases the risk of skin cancer and early skin aging caused by the sun

Warnings

For external use only

Do not use on damaged or broken skin

When using this product keep out of eyes. Rinse with water to remove

Stop use and ask a doctor if rash occurs

Keep out of reach of children. If swallowed, get medical help or contact a Poison Control Center right away.

Directions

apply generously 15 minutes before sun exposure

children under 6 months of age: Ask a doctor

reapply at least every 2 hours

use a water resistant sunscreen if swimming or sweating

Sun Protection Measures. Spending time in the sun increases your risk of skin cancer and early skin aging. To decrease this risk, regularly use a sunscreen with a Broad Spectrum SPF value of 15 or higher and other sun protection measures including: • limit time in the sun, especially from 10 a.m.-2 p.m. • wear long-sleeved shirts, pants, hats and sunglasses

OTHER SAFETY INFORMATION

protect the product in this container from excessive heat and direct sun

INACTIVE INGREDIENT

Inactive ingredients AQUA/WATER/EAU, CYCLOPENTASILOXANE, C12-15 ALKYL BENZOATE, DIMETHICONE, GLYCERIN, CYCLOHEXASILOXANE, POLYGLYCERYL-3 POLYDIMETHYLSILOXYETHYL DIMETHICONE, DIMETHICONE/PEG-10/15 CROSSPOLYMER, ALUMINUM HYDROXIDE, HELIANTHUS ANNUUS (SUNFLOWER) SEED OIL, STEARIC ACID, SODIUM CHLORIDE, CETYL PEG/PPG-10/1 DIMETHICONE, HEXYL LAURATE, POLYGLYCERYL-4 ISOSTEARATE, PHENOXYETHANOL, DIMETHICONE/POLYGLYCERIN-3 CROSSPOLYMER, CITRUS AURANTIUM DULCIS (ORANGE) PEEL OIL, IRON OXIDES (CI 77492), LIMONENE, CAPRYLYL GLYCOL, CETEARYL OLIVATE, TRIETHOXYSILYLETHYL POLYDIMETHYLSILOXYETHYL HEXYL DIMETHICONE, SORBITAN OLIVATE, DIMETHICONE/VINYL DIMETHICONE CROSSPOLYMER, ETHYLHEXYLGLYCERIN, HEXYLENE GLYCOL, CITRUS NOBILIS (MANDARIN ORANGE) PEEL OIL, TOCOPHERYL ACETATE, IRON OXIDES (CI 77491), CAMELLIA SINENSIS LEAF EXTRACT, IRON OXIDES (CI 77499), BENZOIC ACID, DIPROPYLENE GLYCOL, TITANIUM DIOXIDE (CI 77891), ARTEMISIA VULGARIS EXTRACT, LAMINARIA DIGITATA EXTRACT, VANILLA PLANIFOLIA FRUIT EXTRACT, TRIETHOXYCAPRYLYLSILANE, SODIUM CITRATE, GLUCOSE, HYDROLYZED PEA PROTEIN, TOCOPHEROL, BAROSMA BETULINA LEAF OIL, TETRAHEXYLDECYL ASCORBATE, ALUMINA, MAGNESIUM OXIDE, SODIUM SUCCINATE, POTASSIUM SORBATE, SODIUM BENZOATE, LECITHIN, PENTAERYTHRITYL TETRA-DI-T-BUTYL HYDROXYHYDROCINNAMATE, SODIUM FERROCYANIDE, ARABIDOPSIS THALIANA EXTRACT, MICROCOCCUS LYSATE, PLANKTON EXTRACT, ERGOTHIONEINE.